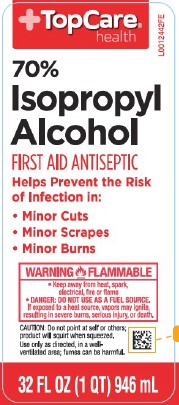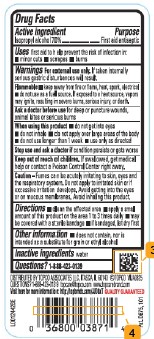 DRUG LABEL: 70% Isopropyl Rubbing Alcohol
NDC: 36800-589 | Form: SOLUTION
Manufacturer: Topco Associates LLC
Category: otc | Type: HUMAN OTC DRUG LABEL
Date: 20260211

ACTIVE INGREDIENTS: ISOPROPYL ALCOHOL 70 mL/100 mL
INACTIVE INGREDIENTS: WATER

Top Care 810.003/810AA
70% Isopropyl Rubbing Alcohol

Active ingredient

Isopropyl Alcohol 70%

Purpose

First Aid Antiseptic

Uses

first aid to help prevent the risk of infection in:

- minor cuts
- scrapes
- burns

Warnings

For external use only. If taken internally serious gastric disturbances will result.

Flammable

- keep away from fire or flame, heat, spark, electrical
- do not use as a fuel source. If exposed to a heat source, vapors may ignite, resulting in severe burns, serious injury, or death.

Ask a doctor before use

for deep or puncture wounds, animal bites or serious burns

When using this product

- do not get into eyes
- do not inhale
- do not apply over large areas of the body
- do not use longer than 1 week
- use only as directed

Stop use and ask a doctor if

condition persists or gets worse

Keep out of reach of children.

If swallowed, get medical help or contact a Poison Control Center right away.

Caution

Fumes can be acutely irritating to skin, eyes and the respiratory system. Do not apply to irritated skin or if excessive irritation develops. Avoid getting into the eyes or on mucous membranes. Avoid inhaling this product.

Directions

- Clean the affected area
- Apply a small amount of this product on the affected area 1 to 3 times daily
- May be covered with a sterile bandage
- If bandaged, let dry first

Other information

- Does not contain, nor is intended as a substitute for grain or ethyl alcohol

Inactive ingredient

water

Questions?

Call 1-888-423-0139

ADVERSE REACTION

DISTRIBUTED BY TOPCO ASSOCIATES LLC, ITASCA, IL 60143 ©TOPCO

QUESTIONS? 1-888-423-0139 topcare@topco.com www.topcarebrand.com

Visit here for more information: http://topbrnds.com QUALITY GUARANTEED

Pat. D675, 101

Principal display panel

TopCare®

health

70% Isopropyl Alcohol

FIRST AID ANTISEPTIC

Helps prevent the Risk of Infection in:

- Minor Cuts
- Minor Scrapes
- Minor Burns

WARNING FLAMMABLE

- Keep away from heat, spark, electrical, fire or flame
- DANGER: DO NOT USE AS A FUEL SOURCE

If exposed to a heat source, vapors may ignite, resulting in severe burns, serious injury, or death.

Caution: Do not point at self or others; product will squirt when squeezed.

Use only as directed, in a well-ventilated area; fumes may be harmful

32 FL OZ (1 QT) 946 mL